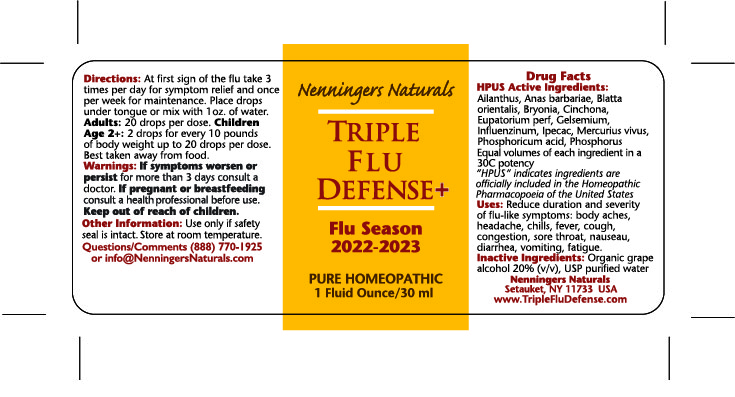 DRUG LABEL: Triple Flu Defense
NDC: 42731-081 | Form: LIQUID
Manufacturer: Nenningers Naturals, LLC
Category: homeopathic | Type: HUMAN OTC DRUG LABEL
Date: 20241218

ACTIVE INGREDIENTS: OYSTER SHELL CALCIUM CARBONATE, CRUDE 30 [hp_C]/30 mL; PHYTOLACCA DODECANDRA WHOLE 30 [hp_C]/30 mL; CAIRINA MOSCHATA HEART/LIVER AUTOLYSATE 30 [hp_C]/30 mL; BRYONIA ALBA ROOT 30 [hp_C]/30 mL; GELSEMIUM SEMPERVIRENS ROOT 30 [hp_C]/30 mL; IPECAC 30 [hp_C]/30 mL; PHOSPHORUS 30 [hp_C]/30 mL; PHOSPHORIC ACID 30 [hp_C]/30 mL; INFLUENZA A VIRUS A/BRISBANE/02/2018 (H1N1) RECOMBINANT HEMAGGLUTININ ANTIGEN 30 [hp_C]/30 mL; INFLUENZA A VIRUS A/KANSAS/14/2017 (H3N2) RECOMBINANT HEMAGGLUTININ ANTIGEN 30 [hp_C]/30 mL; INFLUENZA B VIRUS B/COLORADO/06/2017 LIVE (ATTENUATED) ANTIGEN 30 [hp_C]/30 mL; INFLUENZA B VIRUS B/PHUKET/3073/2013 RECOMBINANT HEMAGGLUTININ ANTIGEN 30 [hp_C]/30 mL; EUPATORIUM PERFOLIATUM FLOWERING TOP 30 [hp_C]/30 mL; CALCIUM SULFIDE 30 [hp_C]/30 mL; CINCHONA OFFICINALIS BARK 30 [hp_C]/30 mL
INACTIVE INGREDIENTS: ALCOHOL; WATER

Triple Flu Defense- 30ML New Updated June 2023

Active Ingredients: Purpose

Anas barbariae 30C HPUS general flu symptoms

Antimonium tart 30C HPUS cough, congestion

Arnica 30C HPUS body aches

Bryonia 30C HPUS body aches, headache

Blatta orientalis 30C HPUS. anti-asthmatic

Eupatorium perf. 30C HPUS general flu symptoms

Ferrum phos 30C HPUS fever, sore throat

Gelsemium 30C HPUS chills, fever, fatigue

Influenzinum 30C HPUS general flu symptoms

Ipecacuanha 30C HPUS nausea, vomiting

Nux Vomica 30C HPUS fever, allergy

Phosphorus 30C HPUS diarrhea, vomiting

Phosphoric acid 30C HPUS fatigue, headache

Pulsatilla 30C HPUS nasal congestion/discharge

Inactive Ingredients:

Organic grape alcohol 20% (v/v),

USP purified Water

Uses:

To reduce the duration and severity of flu-like symptoms: body aches, headache, sore throat, cough, congestion, fever, chills, nausea, diarrhea, vomiting, fatigue.

Warnings:

If symptoms worsen or persist for more than 3 days consult a physician.

If pregnant or breastfeeding consult a physician before use.

Keep out of reach of children.

Directions:

At the first sign of the flu, take 3 times per day for symptom relief and once weekly for maintenance.

Place drops on the tongue or mix with one ounce of water.

Adult Dose is 20 drops per dose. Children under 12 take 2 drops for every 10 pounds of body weight up to a maximum of 20 drops per dose.

Other information:

Use only if safety seal is intact. Store at room temperature.

Package size: 30 mL NDC: 42731-081-01